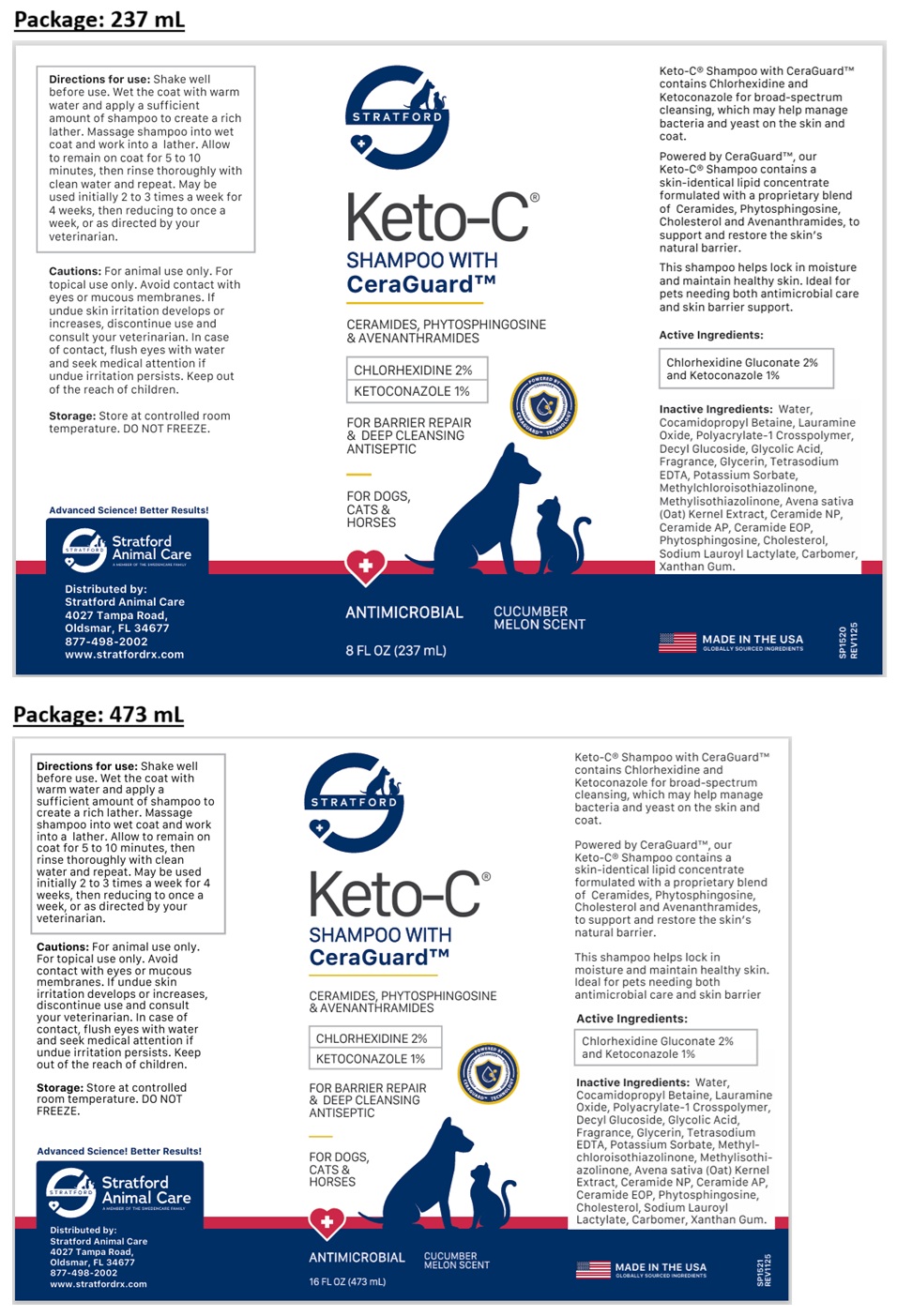 DRUG LABEL: STRATFORD Keto-C WITH CeraGuard
NDC: 86069-135 | Form: SHAMPOO
Manufacturer: Stratford Care Usa, Inc.
Category: animal | Type: OTC ANIMAL DRUG LABEL
Date: 20260108

ACTIVE INGREDIENTS: CHLORHEXIDINE GLUCONATE 2 g/100 mL; KETOCONAZOLE 1 g/100 mL
INACTIVE INGREDIENTS: WATER; COCAMIDOPROPYL BETAINE; LAURAMINE OXIDE; POLYACRYLATE-1 CROSSPOLYMER; DECYL GLUCOSIDE; GLYCOLIC ACID; GLYCERIN; EDETATE SODIUM; POTASSIUM SORBATE; METHYLCHLOROISOTHIAZOLINONE; METHYLISOTHIAZOLINONE; OAT; CERAMIDE NP; CERAMIDE AP; CERAMIDE 9; PHYTOSPHINGOSINE; CHOLESTEROL; SODIUM LAUROYL LACTYLATE; CARBOMER HOMOPOLYMER, UNSPECIFIED TYPE; XANTHAN GUM

STRATFORD Keto-C® SHAMPOO WITH CeraGuardTM

Keto-C® Shampoo with CeraGuard™ contains Chlorhexidine and Ketoconazole for broad-spectrum cleansing, which may help manage bacteria and yeast on the skin and coat.

Powered by CeraGuard™, our Keto-C® Shampoo contains a skin-identical lipid concentrate formulated with a proprietary blend of Ceramides, Phytosphingosine, Cholesterol and Avenanthramides, to support and restore the skin’s natural barrier.

This shampoo helps lock in moisture and maintain healthy skin. Ideal for pets needing both antimicrobial care and skin barrier support.

Active Ingredients:

Chlorhexidine Gluconate 2% and Ketoconazole 1%

Inactive Ingredients:

Water, Cocamidopropyl Betaine, Lauramine Oxide, Polyacrylate-1 Crosspolymer, Decyl Glucoside, Glycolic Acid, Fragrance, Glycerin, Tetrasodium EDTA, Potassium Sorbate, Methylchloroisothiazolinone, Methylisothiazolinone, Avena sativa (Oat) Kernel Extract, Ceramide NP, Ceramide AP, Ceramide EOP, Phytosphingosine, Cholesterol, Sodium Lauroyl Lactylate, Carbomer, Xanthan Gum.

Directions for use:

Shake well before use. Wet the coat with warm water and apply a sufficient amount of shampoo to create a rich lather. Massage shampoo into wet coat and work into a lather. Allow to remain on coat for 5 to 10 minutes, then rinse thoroughly with clean water and repeat. May be used initially 2 to 3 times a week for 4 weeks, then reducing to once a week, or as directed by your veterinarian.

Cautions:

For animal use only. For topical use only. Avoid contact with eyes or mucous membranes. If undue skin irritation develops or increases, discontinue use and consult your veterinarian. In case of contact, flush eyes with water and seek medical attention if undue irritation persists. Keep out of the reach of children.

Storage:

Store at controlled room temperature. DO NOT FREEZE.

CERAMIDES, PHYTOSPHINGOSINE & AVENANTHRAMIDES

FOR BARRIER REPAIR & DEEP CLEANSING ANTISEPTIC

FOR DOGS, CATS & HORSES

ANTIMICROBIAL

CUCUMBER MELON SCENT

MADE IN THE USA
GLOBALLY SOURCED INGREDIENTS

Advanced Science! Better Results!

Stratford Animal Care
A MEMBER OF THE SWEDENCARE FAMILY

Distributed by:
Stratford Animal Care
4027 Tampa Road,
Oldsmar, FL 34677
877-498-2002
www.stratfordrx.com